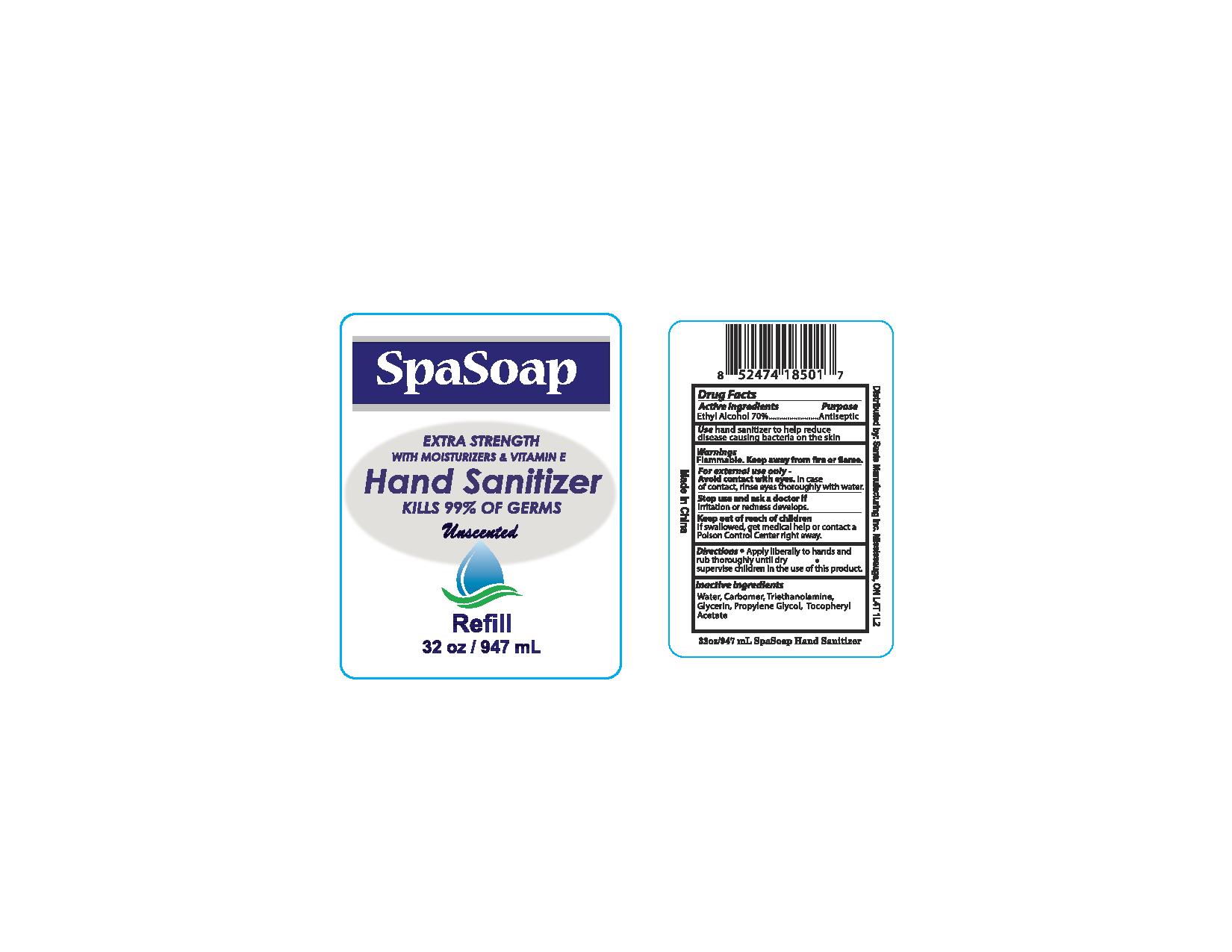 DRUG LABEL: Unscented
NDC: 71020-014 | Form: LIQUID
Manufacturer: Sante Manufacturing Inc
Category: otc | Type: HUMAN OTC DRUG LABEL
Date: 20170311

ACTIVE INGREDIENTS: ALCOHOL 700 mL/1000 mL
INACTIVE INGREDIENTS: GLYCERIN; WATER; CARBOMER 940; .ALPHA.-TOCOPHEROL ACETATE

Active Ingredients - ethyl Alcohol 70%

Purpose - Antiseptic

INDICATIONS AND USAGE

Use hand sanitizer to help reduce disease causing bacteria on the skin

WARNINGS

Flammable

OTHER SAFETY INFORMATION

Keep Away from fire or flame

GENERAL PRECAUTIONS

For external use only

WHEN USING

Avoid Contact with eyes. In case of contact, rinse eyes thoroughly with water

Stop use and ask a doctor if irritation or redness develops

Keep out of reach of children

If swallowed, get medical help or contact a Poison Control Center right away

Directions

- Apply liberally to hands and rub thoroughly until dry
- Supervise children in the use of this product

INACTIVE INGREDIENT

Water, Carbomer, Triethanolamine, Glycerin, Propylene Glycol, Tocopheryl Acetate

PACKAGE LABEL

SpaSoap

Extra Strength with Moisturizers & Vitamin E

Hand Sanitizer

Kills 99% of Germs

Unscented

Refill

32oz / 947ml